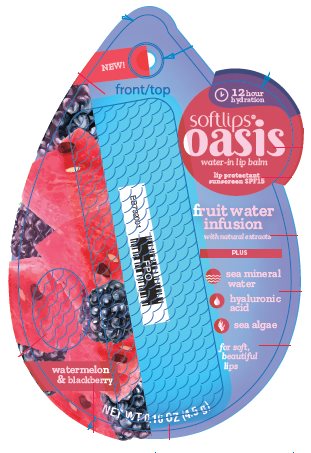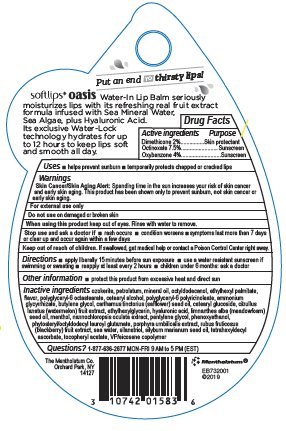 DRUG LABEL: Softlips Oasis Watermelon Blackberry
NDC: 10742-8747 | Form: STICK
Manufacturer: The Mentholatum Company
Category: otc | Type: HUMAN OTC DRUG LABEL
Date: 20241217

ACTIVE INGREDIENTS: DIMETHICONE 20 mg/1 g; OCTINOXATE 75 mg/1 g; OXYBENZONE 40 mg/1 g
INACTIVE INGREDIENTS: CERESIN; PETROLATUM; MINERAL OIL; OCTYLDODECANOL; ETHYLHEXYL PALMITATE; POLYGLYCERYL-6 DISTEARATE; CETOSTEARYL ALCOHOL; POLYGLYCERYL-3 RICINOLEATE; AMMONIUM GLYCYRRHIZATE; BUTYLENE GLYCOL; SAFFLOWER OIL; CETEARYL GLUCOSIDE; WATERMELON; ETHYLHEXYLGLYCERIN; HYALURONIC ACID; MEADOWFOAM SEED OIL; MENTHOL, UNSPECIFIED FORM; PHYMATOLITHON CALCAREUM; PENTYLENE GLYCOL; PHENOXYETHANOL; PHYTOSTERYL/OCTYLDODECYL LAUROYL GLUTAMATE; PORPHYRA UMBILICALIS; BLACKBERRY; SODIUM CHLORIDE; SILANETRIOL; SILYBUM MARIANUM SEED OIL; TETRAHEXYLDECYL ASCORBATE; .ALPHA.-TOCOPHEROL ACETATE; EICOSYL POVIDONE

Drug Facts - Softlips Oasis Watermelon Blackberry

Active ingredient

Dimethicone 2%

Octinoxate 7.5%

Oxybenzone 4%

Purpose

Dimethicone - Skin protectant

Octinoxate - Sunscreen

Oxybenzone – Sunscreen

Uses

- helps prevent sunburn
- temporarily protects chapped or cracked lips

Warnings

Skin Cancer/Skin Aging Alert: Spending time in the sun increases your risk of skin cancer and early skin aging. This product has been shown only to prevent sunburn, not skin cancer or early skin aging.

For external use only

Do not use

on damaged or broken skin

When using this product

keep out of eyes. Rinse with water to remove.

Stop use and ask a doctor if

- rash occurs
- condition worsens
- symptoms last more than 7 days or clear up and occur again within a few days

Keep Out of Reach of Children

If swallowed, get medical help or contact a Poison Control Center right away.

Directions

- apply liberally 15 minutes before sun exposure
- use a water resistant sunscreen if swimming or sweating
- reapply at least every 2 hours
- children under 6 months: ask a doctor

Inactive ingredients

ozokerite, petrolatum, mineral oil, octyldodecanol, ethylhexyl palmitate, flavor, polyglyceryl-6 octastearate, cetearyl alcohol, polyglyceryl-6 polyricinoleate, ammonium glycyrrhizate, butylene glycol, carthamus tinctorius (safflower) seed oil, cetearyl glucoside, citrullus lanatus (watermelon) fruit extract, ethylhexylglycerin, hyaluronic acid, limnanthes alba (meadowfoam) seed oil, menthol, nannochloropsis oculata extract, pentylene glycol, phenoxyethanol, phytosteryl/octyldodecyl lauroyl glutamate, porphyra umbilicalis extract, rubus fruticosus (blackberry) fruit extract, sea water, silanetriol, silybum marianum seed oil, tetrahexyldecyl ascorbate, tocopheryl acetate, VP/eicosene copolymer